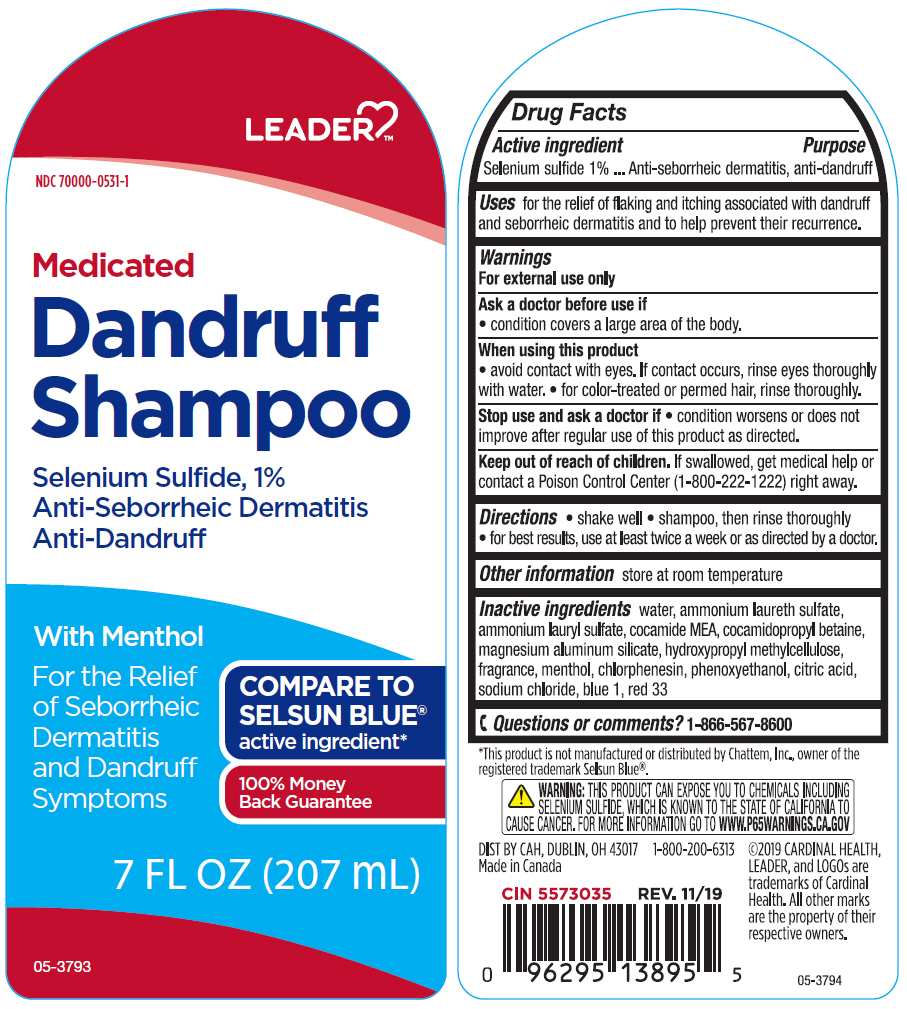 DRUG LABEL: Leader Medicated Dandruff
NDC: 70000-0531 | Form: SHAMPOO
Manufacturer: Cardinal Health, 110 dba LEADER
Category: otc | Type: HUMAN OTC DRUG LABEL
Date: 20240313

ACTIVE INGREDIENTS: Selenium Sulfide 10 mg/1 mL
INACTIVE INGREDIENTS: Water; AMMONIUM LAURETH-5 SULFATE; Ammonium Lauryl Sulfate; COCO MONOETHANOLAMIDE; Cocamidopropyl Betaine; Magnesium Aluminum Silicate; HYPROMELLOSE, UNSPECIFIED; MENTHOL, UNSPECIFIED FORM; Chlorphenesin; Phenoxyethanol; CITRIC ACID MONOHYDRATE; Sodium Chloride; FD&C BLUE NO. 1; D&C RED NO. 33

Leader™ Medicated Dandruff Shampoo
Anti-Seborrheic Dermatitis, Anti-Dandruff

Drug Facts

Active ingredient

Selenium Sulfide 1%

Purpose

Anti-seborrheic dermatitis, anti-dandruff

Uses

for the relief of flaking and itching associated with dandruff and seborrheic dermatitis and to help prevent their recurrence.

Warnings

For external use only

As a doctor before use if

- condition covers a large area of the body.

When using this product

- avoid contact with the eyes. If contact occurs, rinse eyes thoroughly with water.
- for color-treated or permed hair, rinse thoroughly.

Stop use and ask a doctor if

- condition worsens or does not improve after regular use of this product as directed.

Keep out of reach of children. If swallowed, get medical help or contact a Poison Control Center (1-800-222-1222) right away.

Directions

- shake well
- shampoo, then rinse thoroughly
- for best results, use at least twice a week or as directed by a doctor.

Other information

store at room temperature

Inactive ingredients

water, ammonium laureth sulfate, ammonium lauryl sulfate, cocamide MEA, cocamidopropyl betaine, magnesium aluminum silicate, hydroxypropyl methylcellulose, fragrance, menthol, chlorphenesin, phenoxyethanol, citric acid, sodium chloride, blue 1, red 33

Questions or comments?

1-866-567-8600

DIST BY CAH, DUBLIN, OH 43017

PRINCIPAL DISPLAY PANEL - 207 mL Bottle Label

LEADER™

NDC 70000-0531-1

Medicated
Dandruff
Shampoo

Selenium Sulfide, 1%
Anti-Seborrheic Dermatitis
Anti-Dandruff

With Menthol

For the Relief
of Seborrheic
Dermatitis
and Dandruff
Symptoms

COMPARE TO
SELSUN BLUE®
active ingredient*

100% Money
Back Guarantee

7 FL OZ (207 mL)

05-3793